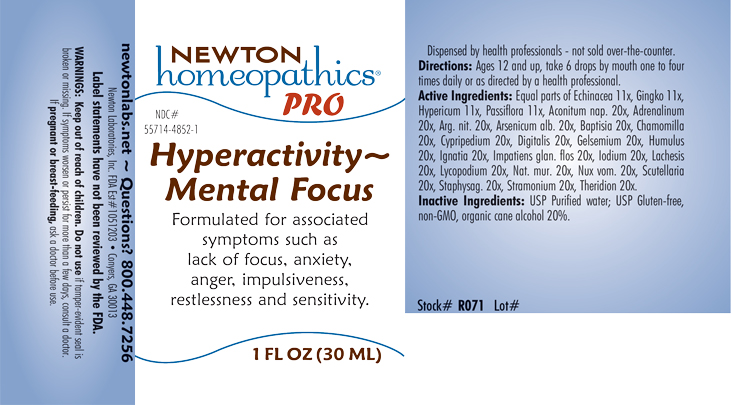 DRUG LABEL: Hyperactivity-Mental Focus
NDC: 55714-4852 | Form: LIQUID
Manufacturer: Newton Laboratories, Inc.
Category: homeopathic | Type: HUMAN OTC DRUG LABEL
Date: 20230623

ACTIVE INGREDIENTS: EPINEPHRINE 20 [hp_X]/1 mL; ACONITUM NAPELLUS 20 [hp_X]/1 mL; SILVER NITRATE 20 [hp_X]/1 mL; ARSENIC TRIOXIDE 20 [hp_X]/1 mL; BAPTISIA TINCTORIA ROOT 20 [hp_X]/1 mL; MATRICARIA CHAMOMILLA 20 [hp_X]/1 mL; CYPRIPEDIUM PARVIFLORUM VAR. PUBESCENS ROOT 20 [hp_X]/1 mL; DIGITALIS 20 [hp_X]/1 mL; GELSEMIUM SEMPERVIRENS ROOT 20 [hp_X]/1 mL; HOPS 20 [hp_X]/1 mL; STRYCHNOS IGNATII SEED 20 [hp_X]/1 mL; IMPATIENS GLANDULIFERA FLOWER 20 [hp_X]/1 mL; IODINE 20 [hp_X]/1 mL; LACHESIS MUTA VENOM 20 [hp_X]/1 mL; LYCOPODIUM CLAVATUM SPORE 20 [hp_X]/1 mL; SODIUM CHLORIDE 20 [hp_X]/1 mL; STRYCHNOS NUX-VOMICA SEED 20 [hp_X]/1 mL; SCUTELLARIA LATERIFLORA WHOLE 20 [hp_X]/1 mL; DELPHINIUM STAPHISAGRIA SEED 20 [hp_X]/1 mL; DATURA STRAMONIUM 20 [hp_X]/1 mL; THERIDION CURASSAVICUM 20 [hp_X]/1 mL; ECHINACEA, UNSPECIFIED 11 [hp_X]/1 mL; GINKGO 11 [hp_X]/1 mL; HYPERICUM PERFORATUM 11 [hp_X]/1 mL; PASSIFLORA INCARNATA FLOWERING TOP 11 [hp_X]/1 mL
INACTIVE INGREDIENTS: WATER; ALCOHOL

Hyperactivity 4852L

INDICATIONS & USAGE SECTION

Formulated for associated symptoms such as lack of focus, anxiety, anger, impulsiveness, restlessness and sensitivity.

DOSAGE & ADMINISTRATION SECTION

Directions: Ages 12 and up, take 6 drops by mouth (ages 0 to 11, give 3 drops) one to four times daily or as directed by a health professional.

OTC - ACTIVE INGREDIENT SECTION

Equal parts of Echinacea 11x, Gingko biloba 11x, Hypericum perforatum 11x, Passiflora incarnata 11x, Aconitum napellus 20x, Adrenalinum 20x, Argentum nitricum 20x, Arsenicum album 20x, Baptisia tinctoria 20x, Chamomilla 20x, Cypripedium pubescens 20x, Digitalis purpurea 20x, Gelsemium sempervirens 20x, Humulus lupulus 20x, Ignatia amara 20x, Impatiens glandulifera flos 20x, Iodium 20x, Lachesis mutus 20x, Lycopodium clavatum 20x, Natrum muriaticum 20x, Nux vomica 20x, Scutellaria lateriflora 20x, Staphysagria 20x, Stramonium 20x, Theridion 20x.

OTC - PURPOSE SECTION

Formulated for associated symptoms such as lack of focus, anxiety, anger, impulsiveness, restlessness and sensitivity.

INACTIVE INGREDIENT SECTION

Inactive Ingredients: USP Purified Water; USP Gluten-free, non-GMO, organic cane alcohol 20%.

QUESTIONS SECTION

newtonlabs.net – Questions? 800.448.7256

Newton Laboratories, Inc. FDA Est # 1051203 - Conyers, GA 30013

WARNINGS SECTION

WARNINGS: Keep out of reach of children. Do not use if tamper-evident seal is broken or missing. If symptoms worsen or persist for more than a few days, consult a doctor. If pregnant or breast-feeding, ask a doctor before use.

OTC - PREGNANCY OR BREAST FEEDING SECTION

If pregnant or breast-feeding, ask a doctor before use.

OTC - KEEP OUT OF REACH OF CHILDREN SECTION

Keep out of reach of children.